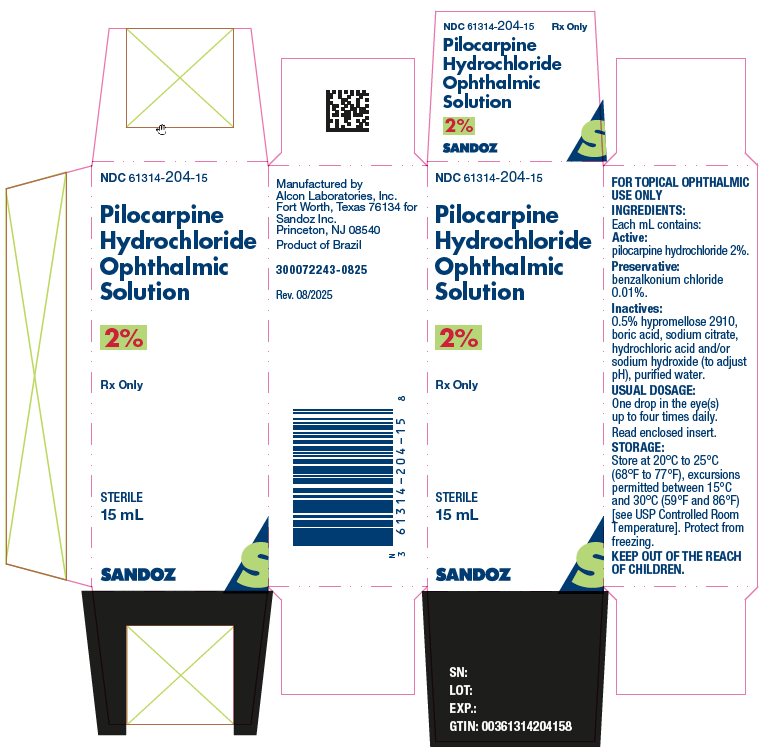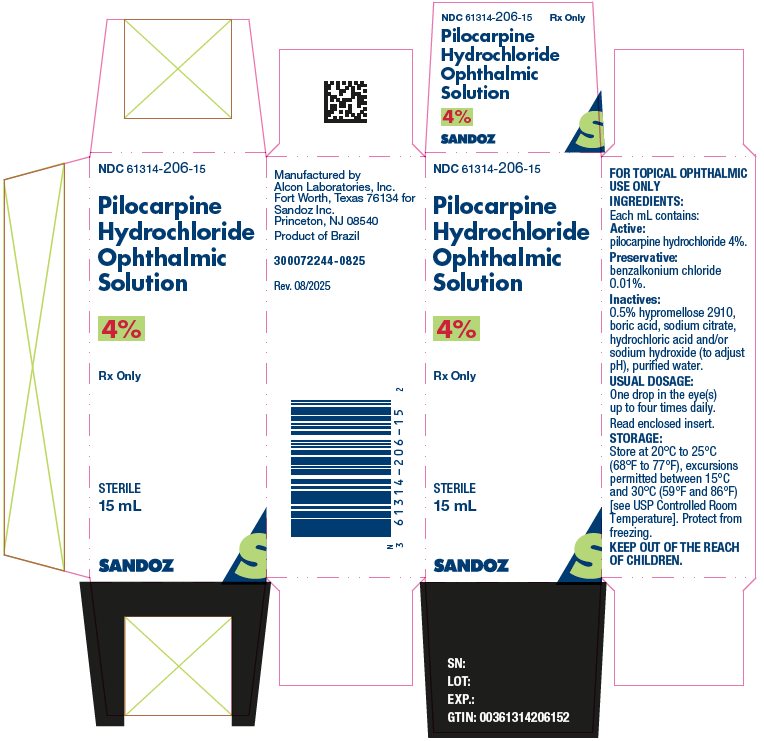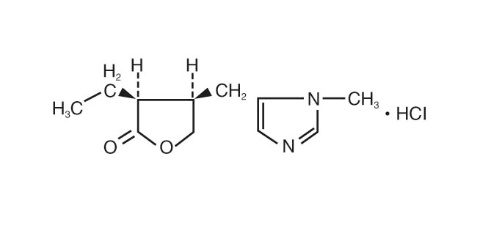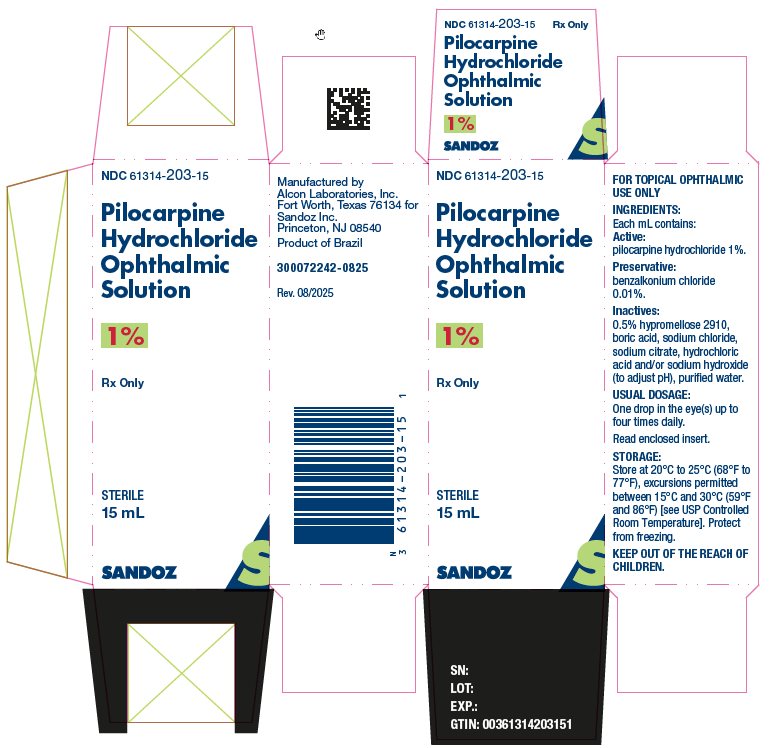 DRUG LABEL: Pilocarpine Hydrochloride
NDC: 61314-203 | Form: SOLUTION/ DROPS
Manufacturer: Sandoz Inc
Category: prescription | Type: HUMAN PRESCRIPTION DRUG LABEL
Date: 20200519

ACTIVE INGREDIENTS: Pilocarpine Hydrochloride 10 mg/1 mL
INACTIVE INGREDIENTS: Benzalkonium Chloride; Hypromellose 2910 (15 Mpa.s); Boric Acid; SODIUM CITRATE, UNSPECIFIED FORM; Sodium Chloride; Hydrochloric Acid; Sodium Hydroxide; Water

HIGHLIGHTS OF PRESCRIBING INFORMATION

These highlights do not include all the information needed to use PILOCARPINE HYDROCHLORIDE OPHTHALMIC SOLUTION safely and effectively. See full prescribing information for PILOCARPINE HYDROCHLORIDE OPHTHALMIC SOLUTION.
PILOCARPINE hydrochloride ophthalmic solution
Initial U.S. Approval: 1974

1 INDICATIONS AND USAGE

Pilocarpine hydrochloride ophthalmic solution is a muscarinic cholinergic agonist indicated for:

- The reduction of elevated intraocular pressure (IOP) in patients with open-angle glaucoma or ocular hypertension. (1.1)
- The management of acute angle-closure glaucoma. (1.2)
- The prevention of postoperative elevated IOP associated with laser surgery. (1.3)
- The induction of miosis. (1.4)

2 DOSAGE AND ADMINISTRATION

Instill one drop in the eye(s) up to four times daily. (2)

3 DOSAGE FORMS AND STRENGTHS

- Solution containing 1% (10 mg/mL), 2% (20 mg/mL) or 4% (40 mg/mL) pilocarpine hydrochloride. (3)

4 CONTRAINDICATIONS

None. (4)

5 WARNINGS AND PRECAUTIONS

- Poor Illumination: Exercise caution in night driving and other hazardous occupations in poor illumination. (5.1)
- Preexisting Retinal Disease: Rare cases of retinal detachment have been reported; a thorough examination of the retina, including funduscopy is advised in all patients prior to the initiation of therapy. (5.2)
- Iritis: Caution is advised in patients with iritis. (5.3)
- Congenital Glaucoma: Caution is advised in pediatric patients with primary congenital glaucoma for control of IOP as cases of a paradoxical increase in IOP have been reported. (5.4)

6 ADVERSE REACTIONS

Most common adverse reactions are headache/browache, accommodative change, eye irritation, eye pain, blurred vision, and/or visual impairment. (6.1)

To report SUSPECTED ADVERSE REACTIONS, contact Sandoz Inc. at 1-800-525-8747 or FDA at 1-800-FDA-1088 or www.fda.gov/medwatch.

FULL PRESCRIBING INFORMATION

1 INDICATIONS AND USAGE

Pilocarpine hydrochloride ophthalmic solution is indicated for the:

1.1 Reduction of Elevated Intraocular Pressure (IOP) in Patients With Open-Angle Glaucoma or Ocular Hypertension

.

1.2 Management of Acute Angle-Closure Glaucoma

.

1.3 Prevention of Postoperative Elevated IOP Associated With Laser Surgery

.

1.4 Induction of Miosis

.

2 DOSAGE AND ADMINISTRATION

2.1 Reduction of Elevated IOP in Patients With Open-Angle Glaucoma or Ocular Hypertension

One drop of pilocarpine hydrochloride ophthalmic solution 1%, 2%, or 4% should be applied topically in the eye(s) up to four times daily.
Pilocarpine-naïve patients should be started on the 1% concentration as higher concentrations are often not tolerated initially. The frequency of instillation and concentration of pilocarpine hydrochloride ophthalmic solution are determined by the severity of the elevated intraocular pressure and miotic response of the patient. To limit systemic exposure to pilocarpine, patients may be instructed to perform punctal occlusion for 2 minutes after instillation of pilocarpine hydrochloride ophthalmic solution.

2.2 Management of Acute Angle-Closure Glaucoma

Prior to pilocarpine hydrochloride ophthalmic solution use, treatment with secretory suppressants and hyperosmotic agents may be needed to lower IOP below 50 mmHg and relieve iris ischemia.
For initial management of acute angle-closure glaucoma, one drop of pilocarpine hydrochloride ophthalmic solution 1% or 2% may be applied topically in the eye(s) up to three times over a 30-minute period.
If laser iridoplasty or iridomy is used to break the attack, one drop of pilocarpine hydrochloride ophthalmic solution 4% should be administered prior to the procedure. Following laser iridoplasty, one drop of pilocarpine hydrochloride ophthalmic solution 1% should be administered four times daily until an iridotomy can be performed.

2.3 Prevention of Postoperative Elevated IOP Associated With Laser Surgery

One drop of pilocarpine hydrochloride ophthalmic solution 1%, 2%, or 4% (or two drops administered five minutes apart) should be applied topically in the eye(s) 15 to 60 minutes prior to surgery.

2.4 Induction of Miosis

One drop of pilocarpine hydrochloride ophthalmic solution 1%, 2%, or 4% (or two drops administered five minutes apart) should be applied topically in the eye(s).

2.5 Use With Other Topical Ophthalmic Medications

Pilocarpine hydrochloride ophthalmic solution may be used in combination with beta-blockers, carbonic anhydrase inhibitors, sympathomimetics or hyperosmotic agents. If more than one topical ophthalmic drug is being used, the drugs should be administered at least five minutes apart.

2.6 Use in Pediatric Patients

In children under 2 years of age, one drop of pilocarpine hydrochloride ophthalmic solution 1% should be applied topically in the eye(s) three times daily. Children 2 years of age and over should be dosed as for adults. For the induction of miosis prior to goniotomy or trabeculotomy in children, one drop of pilocarpine hydrochloride ophthalmic solution 1% or 2% should be applied topically in the eye 15 to 60 minutes prior to surgery.

3 DOSAGE FORMS AND STRENGTHS

Bottle filled with 15 mL of 1% (10 mg/mL), 2% (20 mg/mL), or 4% (40 mg/mL) pilocarpine hydrochloride sterile ophthalmic solution.

4 CONTRAINDICATIONS

None.

5 WARNINGS AND PRECAUTIONS

5.1 Poor Illumination

Patients should be advised to exercise caution in night driving and other hazardous occupations in poor illumination. In addition, miotics may cause accommodative spasm. Patients should be advised not to drive or use machinery if vision is not clear.

5.2 Preexisting Retinal Disease

As with all miotics, rare cases of retinal detachment have been reported when used in certain susceptible individuals and those with preexisting retinal disease; therefore, a thorough examination of the retina including funduscopy is advised in all patients prior to the initiation of therapy.

5.3 Iritis

Pilocarpine hydrochloride ophthalmic solution is not recommended to be used when iritis is present.

5.4 Primary Congenital Glaucoma

Caution is advised when using pilocarpine hydrochloride ophthalmic solution in pediatric patients with primary congenital glaucoma for control of IOP as cases of a paradoxical increase in IOP have been reported. In addition, the use of pilocarpine hydrochloride ophthalmic solution is not recommended in pediatric patients diagnosed with glaucoma secondary to anterior segment dysgenesis or uveitis (especially if uveitis is active).

5.5 Contact Lens Wear

Contact lens wearers should be advised to remove their lenses prior to the instillation of pilocarpine hydrochloride ophthalmic solution and to wait 10 minutes after dosing before reinserting their contact lenses.

6 ADVERSE REACTIONS

6.1 Clinical Trials Experience

Because clinical trials are conducted under widely varying conditions, adverse reaction rates observed in the clinical trials of a drug cannot be directly compared to rates in the clinical trials of another drug and may not reflect the rates observed in practice.

The safety data described below reflect exposure in four controlled clinical trials of 90 days to 2 years duration in 317 patients diagnosed with open-angle glaucoma or ocular hypertension. In the four clinical trials, patients were treated with pilocarpine hydrochloride ophthalmic solution 2%, two to four times daily or with pilocarpine 1%, 1.75%, or 2% in fixed combination with betaxolol 0.25%, two or three times daily. The most frequently reported adverse reactions occurring in ≥ 5% of patients in the pilocarpine 2% populations were: headache/brow ache, accommodative change, blurred vision, eye irritation, visual impairment (dim, dark, or “jumping” vision), and eye pain.

The adverse reaction profile reported for the use of pilocarpine hydrochloride ophthalmic solution in pediatric patients is comparable to that seen in adult patients.

8 USE IN SPECIFIC POPULATIONS

8.1 Pregnancy

Animal reproduction studies have not been conducted with pilocarpine hydrochloride. It is also not known whether pilocarpine hydrochloride can cause fetal harm when administered to a pregnant woman or can affect reproduction capacity. Pilocarpine hydrochloride ophthalmic solution should be given to a pregnant woman only if clearly needed.

8.3 Nursing Mothers

It is not known whether this drug is excreted in human milk. Because many drugs are excreted in human milk, caution should be exercised when pilocarpine hydrochloride ophthalmic solution is administered to a nursing woman.

8.4 Pediatric Use

Safety and effectiveness of pilocarpine hydrochloride ophthalmic solution in pediatric patients have been established.

8.5 Geriatric Use

No overall differences in safety or effectiveness have been observed between elderly and younger patients.

10 OVERDOSAGE

Systemic toxicity following topical ocular administration of pilocarpine is rare, but occasionally patients who are sensitive may develop sweating and gastrointestinal overactivity following the suggested dosage and administration. Overdosage can produce sweating, salivation, nausea, tremors and slowing of the pulse and a decrease in blood pressure. In moderate overdosage, spontaneous recovery is to be expected and is aided by intravenous fluids to compensate for dehydration. For patients demonstrating severe poisoning, atropine, the pharmacologic antagonist to pilocarpine, should be used.

11 DESCRIPTION

Pilocarpine hydrochloride ophthalmic solution is a cholinergic agonist prepared as a sterile topical ophthalmic solution. The active ingredient is represented by the chemical structure:

Established name: pilocarpine hydrochloride Chemical name: 2(3H)-furanone, 3-ethyldihydro-4-[(1-methyl-1H-imidazol-5-yl)-methyl]- monohydrochloride, (3S-cis)-. Molecular Formula: C11H16N2O2 • HCl; Molecular Weight: 244.72 g/mol.
Each mL of contains: Active: pilocarpine hydrochloride 1% (10 mg/mL), 2% (20 mg/mL), or 4% (40 mg/mL). Preservative: benzalkonium chloride 0.01%. Inactives: hypromellose 2910, boric acid, sodium citrate, sodium chloride (present in 1% only); hydrochloric acid and/or sodium hydroxide (to adjust pH); purified water. Pilocarpine hydrochloride ophthalmic solution has a pH of 3.5 to 5.5 and an osmolality of 290 to 350 mOsm/kg (1% and 2% products) and 550 to 600 mOsm/kg (4% product).

12 CLINICAL PHARMACOLOGY

12.1 Mechanism of Action

Pilocarpine hydrochloride is a direct acting cholinergic parasympathomimetic agent which acts through direct stimulation of muscarinic receptors and smooth muscle such as the iris and secretory glands. Pilocarpine contracts the ciliary muscle, causing increased tension on the scleral spur and opening of the trabecular meshwork spaces to facilitate outflow of aqueous humor. Outflow resistance is reduced, lowering IOP. Pilocarpine also produces miosis through contraction of the iris sphincter muscle. Miosis relieves appositional angle narrowing and closure, which lowers IOP in certain types of angle-closure glaucoma.

12.3 Pharmacokinetics

Systemic exposure to pilocarpine was evaluated in 14 healthy subjects administered 2 drops of pilocarpine hydrochloride ophthalmic solution 4% to both eyes four times daily for eight days. A comparison of Cmax values on Days 5 and 8 indicated that pilocarpine concentrations in plasma reached steady-state following topical administration of pilocarpine hydrochloride ophthalmic solution 4%. The mean (SD) Cmax and AUC0-last values on Day 8 were 3.7 (3.2) ng/mL and 7.7 (8.4) ng×hour/mL, respectively. The Tmax values on Day 8 ranged from 0.5 to 1 hour.

13 NONCLINICAL TOXICOLOGY

13.1 Carcinogenesis, Mutagenesis, Impairment of Fertility

There have been no long-term studies done using pilocarpine hydrochloride in animals to evaluate carcinogenic potential.

14 CLINICAL STUDIES

In clinical trials reported in the medical literature, pilocarpine ophthalmic solution reduced IOP by 3-7 mmHg in patients with open-angle glaucoma. Pilocarpine ophthalmic solution has also been shown to be effective in the induction of miosis, in the prevention of postoperative elevated IOP, and in the management of acute angle-closure glaucoma.

16 HOW SUPPLIED/STORAGE AND HANDLING

Pilocarpine hydrochloride ophthalmic solution 1%, 2%, and 4% is supplied sterile in natural low density polyethylene plastic ophthalmic dispensers and green low density polyethylene tips with green polypropylene caps.
15 mL in 15 mL bottles
1%: NDC 61314-203-15
2%: NDC 61314-204-15
4%: NDC 61314-206-15
STORAGE: Store at 20°C to 25°C (68°F to 77°F), excursions permitted between 15°C and 30°C (59°F and 86°F) [see USP Controlled Room Temperature]. Protect from freezing.

17 PATIENT COUNSELING INFORMATION

Avoiding Contamination of the Product

Do not touch dropper tip to any surface, as this may contaminate the contents.

Night Driving

Caution is advised with night driving and when hazardous activities are undertaken in poor illumination.

Accommodative Spasm

Pilocarpine hydrochloride ophthalmic solution may cause problems when changing focus between near objects and distant objects. Do not drive or use machinery if vision is not clear.

Contact Lens Wear

Contact lens should be removed prior to the instillation of pilocarpine hydrochloride ophthalmic solution. Wait 10 minutes after dosing before reinserting contact lenses.

Concomitant Topical Ocular Therapy

If more than one topical ophthalmic medication is being used, the medicines must be administered at least 5 minutes apart.

Systemic Exposure

To limit exposure to pilocarpine to the eye alone, close eyes gently and apply pressure with finger to the corner of eye by the nose for 2 minutes after instillation of pilocarpine hydrochloride ophthalmic solution.

update to

Manufactured by

Alcon Laboratories, Inc.

Fort Worth, Texas 76134 for

Sandoz Inc.

Princeton, NJ 08540

T2020-98

300072245-0825

PRINCIPAL DISPLAY PANEL

NDC 61314-203-15
Pilocarpine

Hydrochloride

Ophthalmic

Solution
1%
Rx only
STERILE
15 mL
SANDOZ

NDC 61314-204-15
Pilocarpine

Hydrochloride

Ophthalmic

Solution
2%
Rx only
STERILE
15 mL
SANDOZ

NDC 61314-206-15
Pilocarpine

Hydrochloride

Ophthalmic

Solution
4%
Rx only
STERILE
15 mL
SANDOZ